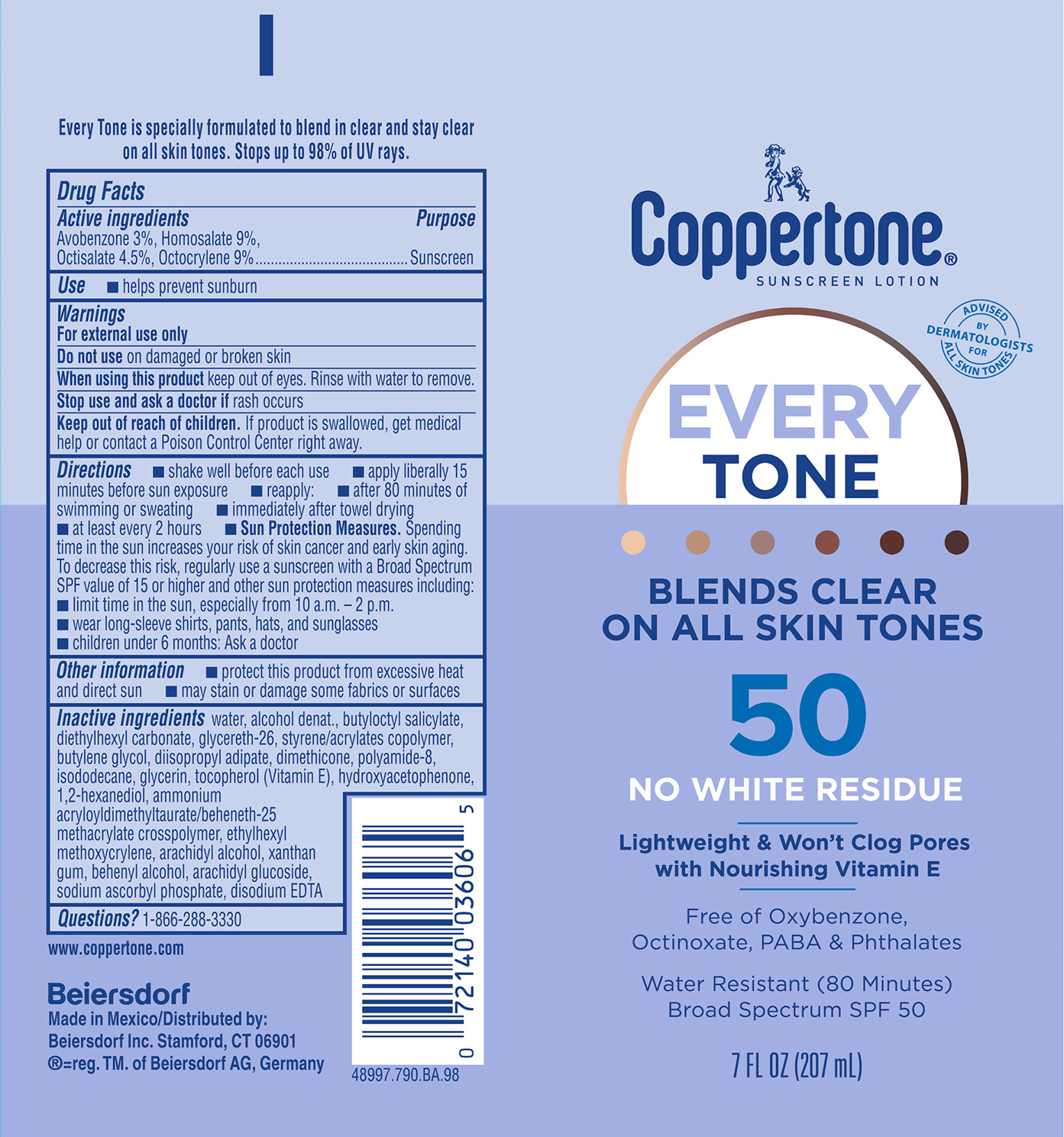 DRUG LABEL: Coppertone Every Tone Sunscreen SPF 50
NDC: 66800-1093 | Form: LOTION
Manufacturer: Beiersdorf Inc
Category: otc | Type: HUMAN OTC DRUG LABEL
Date: 20251231

ACTIVE INGREDIENTS: AVOBENZONE 3 g/100 g; OCTOCRYLENE 9 g/100 g; HOMOSALATE 9 g/100 g; OCTISALATE 4.5 g/100 g
INACTIVE INGREDIENTS: AMMONIUM ACRYLOYLDIMETHYLTAURATE/BEHENETH-25 METHACRYLATE CROSSPOLYMER (52000 MPA.S); DIISOPROPYL ADIPATE; DIMETHICONE; POLYAMIDE-8 (4500 MW); ISODODECANE; TOCOPHEROL; STYRENE/ACRYLAMIDE COPOLYMER (MW 500000); ARACHIDYL GLUCOSIDE; ALCOHOL; GLYCERETH-26; ETHYLHEXYL METHOXYCRYLENE; BUTYLENE GLYCOL; XANTHAN GUM; DOCOSANOL; SODIUM ASCORBYL PHOSPHATE; WATER; BUTYLOCTYL SALICYLATE; DIETHYLHEXYL CARBONATE; HYDROXYACETOPHENONE; DISODIUM EDTA-COPPER; GLYCERIN; 1,2-HEXANEDIOL; ARACHIDYL ALCOHOL

Every Tone Lotion SPF 50

Active ingredients

Avobenzone 3%, Homosalate 9%, Octisalate 4.5%, Octocrylene 9%

Purpose

Sunscreen

Use

■ helps prevent sunburn

Warnings

For external use only

Do not useon damaged or broken skin

WHEN USING

When using this productkeep out of eyes. Rinse with water to remove.

Stop use and ask a doctor ifrash occurs

Keep out of reach of children.If product is swallowed, get medical help or contact a Poison Control Center right away.

Directions

■ shake well before use

■ apply liberally 15 minutes before sun exposure

■ reapply:

■ after 80 minutes of swimming or sweating

■ immediately after towel drying

■ at least every 2 hours

■ Sun Protection Measures.Spending time in the sun increases your risk of skin cancer and early skin aging. To decrease this risk, regularly use a sunscreen with a Broad Spectrum SPF value of 15 or higher and other sun protection measures including:

■ limit time in the sun, especially from 10 a.m. – 2 p.m.

■ wear long-sleeve shirts, pants, hats, and sunglasses

■ children under 6 months: Ask a doctor

Other information

■ protect this product from excessive heat and direct sun

■ may stain or damage some fabrics or surfaces

Inactive ingredients

water, alcohol denat., butyloctyl salicylate, diethylhexyl carbonate, glycereth-26, styrene/acrylates copolymer, butylene glycol, diisopropyl adipate, dimethicone, polyamide-8, isododecane, glycerin, tocopherol (Vitamin E), hydroxyacetophenone, 1,2-hexanediol, ammonium acryloyldimethyltaurate/beheneth-25 methacrylate crosspolymer, ethylhexyl methoxycrylene, arachidyl alcohol, xanthan gum, behenyl alcohol, arachidyl glucoside, sodium ascorbyl phosphate, disodium EDTA

Questions?

1-866-288-3330

PACKAGE LABEL

Coppertone®

Sunscreen Lotion

Advised by Dermatologists for Skin of Color

Every Tone

Blends Clear On All Skin Tones

50

No White Resdiue

Lightweight & Won't Clog Pores

with nourishing Vitamin E

Free of Oxybenzone, Octinoxate, PABA & Phthalates

Water Resistant (80 Minutes)

Broad Spectrum SPF 50